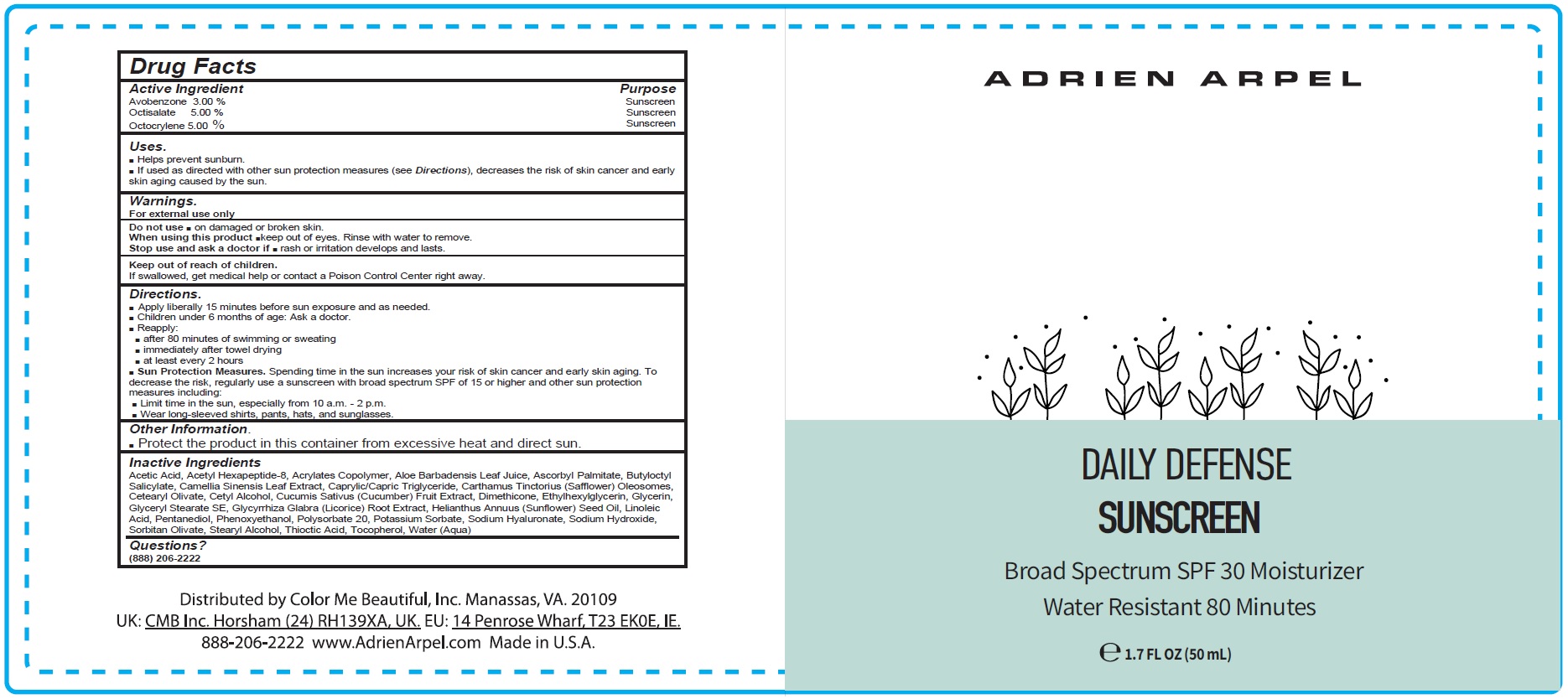 DRUG LABEL: Adrien Arpel Daily Defense Moisturizer SPF 30
NDC: 87372-985 | Form: CREAM
Manufacturer: Color Me Beautiful Inc
Category: otc | Type: HUMAN OTC DRUG LABEL
Date: 20260202

ACTIVE INGREDIENTS: AVOBENZONE 30 mg/1 mL; OCTISALATE 50 mg/1 mL; OCTOCRYLENE 50 mg/1 mL
INACTIVE INGREDIENTS: ACETIC ACID; ACETYL HEXAPEPTIDE-8 AMIDE; ALOE VERA LEAF JUICE; ASCORBYL PALMITATE; BUTYLOCTYL SALICYLATE; GREEN TEA LEAF; MEDIUM-CHAIN TRIGLYCERIDES; CARTHAMUS TINCTORIUS SEED OLEOSOMES; CETEARYL OLIVATE; CETYL ALCOHOL; CUCUMBER; DIMETHICONE; ETHYLHEXYLGLYCERIN; GLYCERIN; GLYCERYL STEARATE SE; GLYCYRRHIZA GLABRA (LICORICE) ROOT POWDER; SUNFLOWER OIL; LINOLEIC ACID; PINANEDIOL; PHENOXYETHANOL; POLYSORBATE 20; POTASSIUM SORBATE; HYALURONATE SODIUM; SODIUM HYDROXIDE; SORBITAN OLIVATE; STEARYL ALCOHOL; ALPHA LIPOIC ACID; TOCOPHEROL; WATER

Adrien Arpel Daily Defense Sunscreen Moisturizer SPF 30

Active Ingredient

Avobenzone 3.00 %
Octisalate 5.00 %
Octocrylene 5.00 %

Purpose

Sunscreen

Uses.

- Helps prevent sunburn.
- If used as directed with other sun protection measures (see Directions), decreases the risk of skin cancer and early skin aging caused by the sun.

Warnings.

For external use only

Do not use

- on damaged or broken skin.

When using this product

- keep out of eyes. Rinse with water to remove.

Stop use and ask a doctor if

- rash or irritation develops and lasts.

Keep out of reach of children.

If swallowed, get medical help or contact a Poison Control Center right away.

Directions.

- Apply liberally 15 minutes before sun exposure and as needed.
- Children under 6 months of age: Ask a doctor.
- Reapply:
- after 80 minutes of swimming or sweating
- immediately after towel drying
- at least every 2 hours
- Sun Protection Measures.Spending time in the sun increases your risk of skin cancer and early skin aging. To decrease the risk, regularly use a sunscreen with broad spectrum SPF of 15 or higher and other sun protection measures including:
- Limit time in the sun, especially from 10 a.m. - 2 p.m.
- Wear long-sleeved shirts, pants, hats, and sunglasses.

Other Information.

- Protect the product in this container from excessive heat and direct sun.

Inactive Ingredients

Acetic Acid, Acetyl Hexapeptide-8, Acrylates Copolymer, Aloe Barbadensis Leaf Juice, Ascorbyl Palmitate, Butyloctyl
Salicylate, Camellia Sinensis Leaf Extract, Caprylic/Capric Triglyceride, Carthamus Tinctorius (Safflower) Oleosomes,
Cetearyl Olivate, Cetyl Alcohol, Cucumis Sativus (Cucumber) Fruit Extract, Dimethicone, Ethylhexylglycerin, Glycerin,
Glyceryl Stearate SE, Glycyrrhiza Glabra (Licorice) Root Extract, Helianthus Annuus (Sunflower) Seed Oil, Linoleic
Acid, Pentanediol, Phenoxyethanol, Polysorbate 20, Potassium Sorbate, Sodium Hyaluronate, Sodium Hydroxide,
Sorbitan Olivate, Stearyl Alcohol, Thioctic Acid, Tocopherol, Water (Aqua)

Questions?

(888) 206-2222